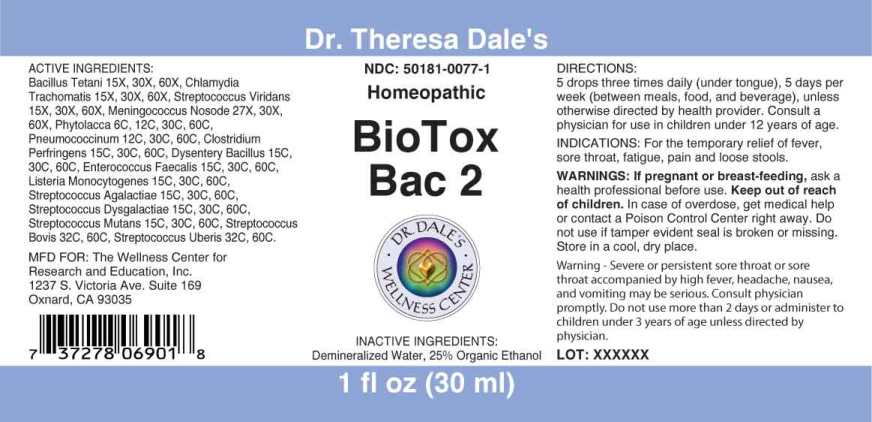 DRUG LABEL: BioTox Bac
NDC: 50181-0077 | Form: LIQUID
Manufacturer: The Wellness Center for Research and Education, Inc.
Category: homeopathic | Type: HUMAN OTC DRUG LABEL
Date: 20250606

ACTIVE INGREDIENTS: CLOSTRIDIUM TETANI 15 [hp_X]/1 mL; CHLAMYDIA TRACHOMATIS 15 [hp_X]/1 mL; STREPTOCOCCUS VIRIDANS GROUP 15 [hp_X]/1 mL; NEISSERIA MENINGITIDIS 27 [hp_X]/1 mL; PHYTOLACCA AMERICANA ROOT 6 [hp_C]/1 mL; STREPTOCOCCUS PNEUMONIAE 12 [hp_C]/1 mL; CLOSTRIDIUM PERFRINGENS 15 [hp_C]/1 mL; SHIGELLA DYSENTERIAE 15 [hp_C]/1 mL; ENTEROCOCCUS FAECALIS 15 [hp_C]/1 mL; LISTERIA MONOCYTOGENES 15 [hp_C]/1 mL; STREPTOCOCCUS AGALACTIAE 15 [hp_C]/1 mL; STREPTOCOCCUS DYSGALACTIAE 15 [hp_C]/1 mL; STREPTOCOCCUS MUTANS 15 [hp_C]/1 mL; STREPTOCOCCUS EQUINUS 32 [hp_C]/1 mL; STREPTOCOCCUS UBERIS 32 [hp_C]/1 mL
INACTIVE INGREDIENTS: WATER; ALCOHOL

DRUG FACTS:

ACTIVE INGREDIENTS:

Bacillus Tetani 15X, 30X, 60X, Chlamydia Trachomatis 15X 30X, 60X, Streptococcus Viridans 15X, 30X, 60, Meningococcus Nosode 27X, 30X, 60X, Phytolacca Decandra 6C, 12C, 30C, 60C, Pneumococcinum 12C, 30C, 60C, Clostridium Perfringens 15C, 30C, 60C, Dysentery Bacillus 15C, 30C, 60C, Enterococcus Faecalis 15C, 30C, 60C, Listeria Monocytogenes 15C, 30C, 60C, Streptococcus Agalactiae 15C, 30C, 60C, Streptococcus Dysgalactiae 15C, 30C, 60C, Streptococcus Mutans 15C, 30C, 60C, Streptococcus Bovis 32C, 60C, Streptococcus Uberis 32C, 60C.

INDICATIONS:

For the temporary relief of fever, sore throat, fatigue, pain and loose stools.

WARNINGS:

If pregnant or breast-feeding, ask a health professional before use.

Keep out of reach of children. In case of overdose, get medical help or contact a Poison Control Center right away.

Do not use if tamper evident seal is broken or missing.

Store in a cool, dry place.

Keep out of reach of children. In case of overdose, get medical help or contact a Poison Control Center right away.

DIRECTIONS:

5 drops three times daily (under tongus), 5 days per week (between meals, food and beverage), unless otherwise directed by health provider.

Consult a physician for use in children under 12 years of age.

INDICATIONS:

For the temporary relief of fever, sore throat, fatigue, pain and loose stools.

INACTIVE INGREDIENTS:

Demineralized Water, 25% Organic Ethanol

QUESTONS:

MFD FOR: The Wellness Center for

Research and Education, Inc.

1237 S. Victoria Ave. Suite 169

Oxnard, CA 93035

PACKAGE LABEL DISPLAY:

Dr. Theresa Dale's

NDC 50181-0077-1

Homeopathic

BioTox Bac 2

1 fl oz (30 ml)